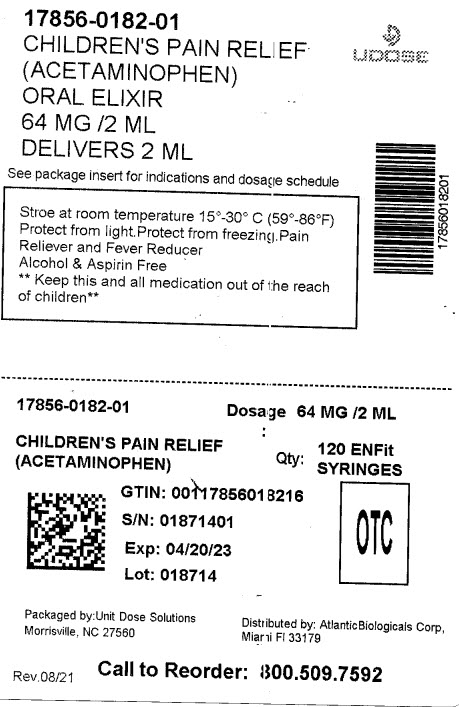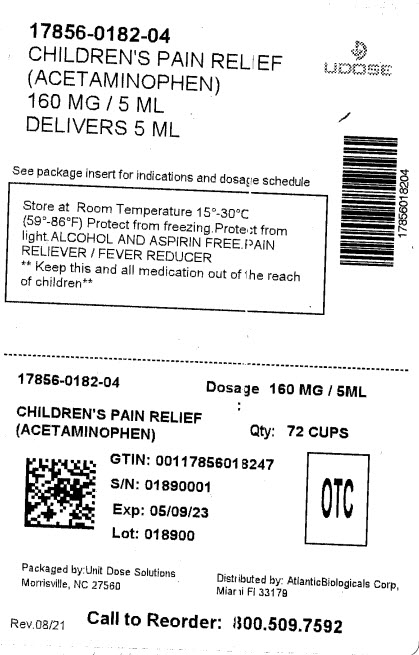 DRUG LABEL: ACETAMINOPHEN
NDC: 17856-0182 | Form: ELIXIR
Manufacturer: ATLANTIC BIOLOGICALS CORP.
Category: otc | Type: HUMAN OTC DRUG LABEL
Date: 20221114

ACTIVE INGREDIENTS: ACETAMINOPHEN 160 mg/5 mL
INACTIVE INGREDIENTS: CITRIC ACID MONOHYDRATE; FD&C RED NO. 40; GLYCERIN; POLYETHYLENE GLYCOL 400; WATER; SODIUM CITRATE; SACCHARIN SODIUM; SORBITOL; SODIUM BENZOATE

Acetaminophen Elxir
Bubble Gum Flavor

Active ingredient (in each 5 mL = 1 teaspoonful)

Acetaminophen 160 mg

Purpose

Pain Reliever/Fever Reducer

Uses

To reduce fever and for the temporary relief of minor aches and pains due to:

- headache
- muscular aches
- backache
- minor pain of arthritis
- the common cold
- toothache
- premenstrual and menstrual cramps.

Temporarily reduces fever.

Warnings

Liver warning

This product contains acetaminophen. Severe liver damage may occur if

- adult takes more than 6 doses in 24 hours, which is the maximum daily amount
- child takes more than 5 doses in 24 hours, which is the maximum daily amount taken with other drugs containing acetaminophen
- adult has 3 or more alcoholic drinks everyday while using this product.

Sore throat warning:

If sore throat is severe, persists for more than 2 days, is accompanied or followed by fever, headache, rash, nausea, or vomiting, consult a doctor promptly.

Do not use

- with any other drug containing acetaminophen (prescription or non-prescription). If you are not sure whether a drug contains acetaminophen, ask a doctor or pharmacist.
- if your child is allergic to acetaminophen or any of the inactive ingredients in this product

Ask a doctor before use if your child has

- liver disease
- is on a sodium-restricted diet.

Ask a doctor or pharmacist before use if your child is taking the blood thinning drug warfarin

When using this product: Do not exceed recommended dose

Stop use and ask a doctor if:

- Pain gets worse or lasts more than 5 days
- fever gets worse or lasts more than 3 days
- new symptoms occur.
- redness or swelling is present.

These could be signs of a serious condition.

PREGNANCY OR BREAST FEEDING

If pregnant or breast-feeding, ask a health professional before use.

Keep out of reach of children.

Overdose Warning:

taking more than the recommended dose (overdose) may cause liver damage.
In case of overdose get medical help or contact a Poison Control Center right away. Quick medical
attention is critical for adults/children even if you do not notice any signs or symptoms.

Directions

- shake well before using
- find the right dose on chart below, if possible, use weight to dose; otherwise use age
- dosage may be repeated every 4 hours, or as directed by your doctor
- do not use more than 5 doses in 24 hours
- do not use more than 5 days unless directed by a doctor.
- find right dose on chart below, If possible, use weight to dose; otherwise, use age.

Weight (lbs.) | Age (years) | dosage-teaspoonful (tsp.)
under 24 | under 2 | consult Physician
24 to 35 | 2 to 3 | 1 tsp. (5 mL)
36 to 47 | 4 to 5 | 1 1/2 tsp. (7.5 mL)
48 to 59 | 6 to 8 | 2 tsp. (10 mL)
60 to 71 | 9 to 10 | 2 1/2 tsp. (12.5 mL)
72 to 95 | 11 | 3 tsp. (15 mL)

Other information

- Store at room temperature 15°-30° C (59°-86°F)
- Protect from Freezing.
- Protect from Light.

TAMPER EVIDENT: DO NOT USE IF BREAKAWAY BAND ON CAP IS BROKEN OR MISSING.

Inactive Ingredients:

Bubble Gum Flavor, Citric Acid, FD C RED #40, Glycerin, Polyethylene Glycol 400, Purified Water, Sodium Citrate, Sodium Saccharin, Sorbitol Solution 70% & Sodium Benzoate.

DISTRIBUTED BY:

ATLANTIC BIOLOGICALS CORP.

MIAMI, FL 33179